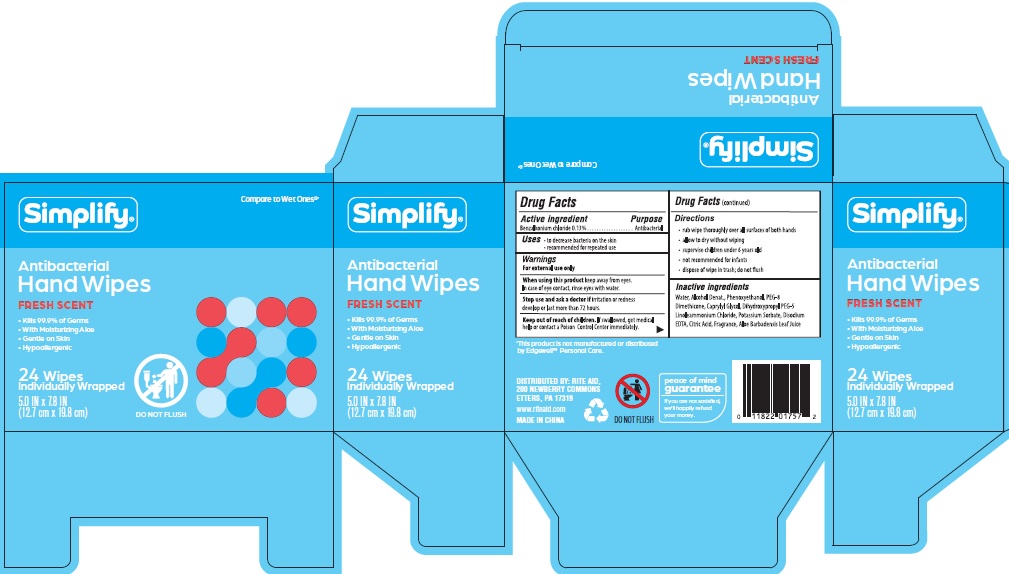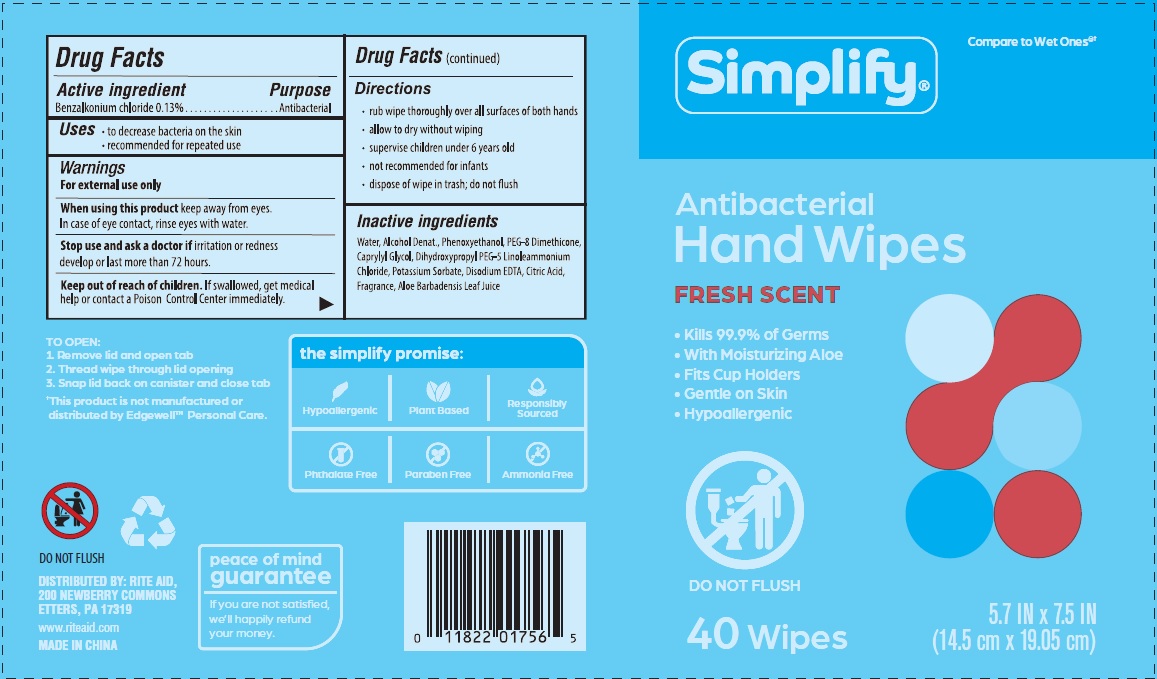 DRUG LABEL: Simplify Antibacterial Hand Wipes
NDC: 11822-0284 | Form: CLOTH
Manufacturer: Rite Aid Corporation
Category: otc | Type: HUMAN OTC DRUG LABEL
Date: 20240729

ACTIVE INGREDIENTS: BENZALKONIUM CHLORIDE 0.13 g/1 1
INACTIVE INGREDIENTS: WATER; ALCOHOL; POTASSIUM SORBATE; PEG-8 DIMETHICONE; CAPRYLYL GLYCOL; CITRIC ACID MONOHYDRATE; ALOE VERA LEAF; EDETATE DISODIUM; PHENOXYETHANOL; DIHYDROXYPROPYL PEG-5 LINOLEAMMONIUM CHLORIDE

Simplify Fresh Scent

Active ingredient

Benzalkonium chloride 0.13%

Purpose

Antibacterial

Uses

- to decrease bacteria on the skin
- recommended for repeated use

Warnings

For external use only

When using this product keep away from eyes. In case of eye contact, rinse eyes with water.

Stop use and ask a doctor if irritation or redness develop or last more than 72 hours.

Keep out of reach of children. If swallowed, get medical help or contact a Poison Control Center immediately.

Directions

- rub wipe thoroughly over all surfaces of both hands
- allow to dry without wiping
- supervise children under 6 years old
- not recommended for infants
- dispose of wipe in trash, do not flush

Inactive ingredients

Water, Alcohol Denat., Phenoxyethanol, PEG-8 Dimethicone, Caprylyl Glycol, Dihydroxypropyl PEG-5 Linoleammonium Chloride, Potassium Sorbate, Disodium EDTA, Citric Acid, Fragrance, Aloe Barbadensis Leaf Juice

DISTRIBUTED BY: RITE AID,

200 NEWBERRY COMMONS

ETTERS, PA 17319

www.riteaid.com

MADE IN CHINA

PDP 11822-0284

Simplify®

Antibacterial

Hand Wipes

FRESH SCENT

Kills 99.9% of Germs

With Moisturizing Aloe

Gentle on skin

Hypoallergenic

DO NOT FLUSH

24 Wipes

Individually Wrapped

5.0 IN x 7.8 IN

(12.7 cm x 19.8 cm)

PDP 11822-0285

Simplify®

Antibacterial

Hand Wipes

FRESH SCENT

Kills 99.9% of Germs

With Moisturizing Aloe

Gentle on skin

Hypoallergenic

DO NOT FLUSH

40 Wipes

5.7 IN x 7.5 IN

(14.5 cm x 19.05 cm)